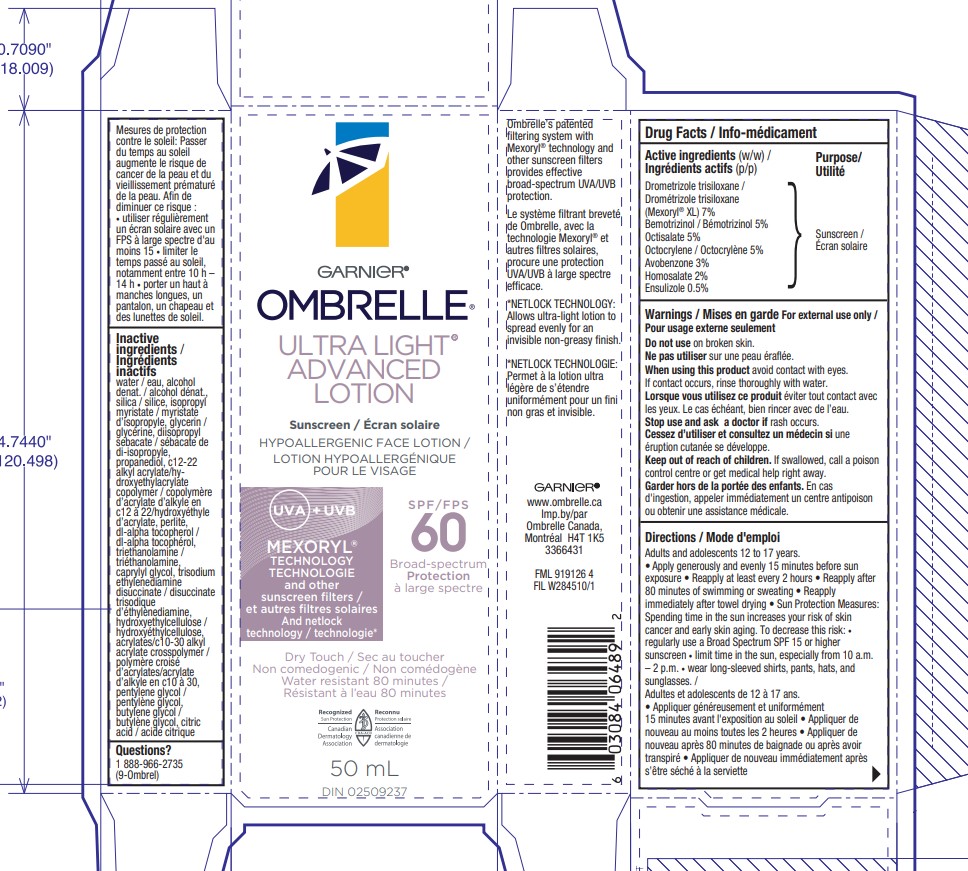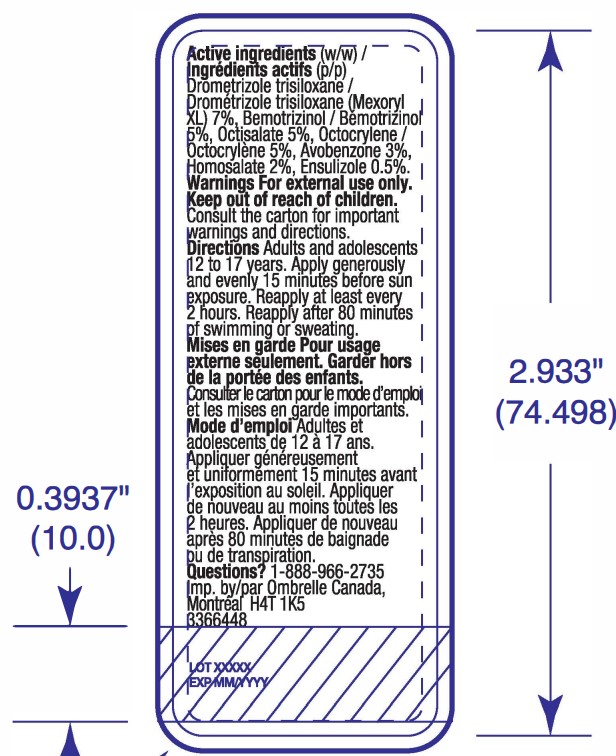 DRUG LABEL: Garnier Ombrelle Ultra Light Advanced Broad Spectrum SPF 60 Sunscreen
NDC: 49967-649 | Form: LOTION
Manufacturer: L'Oreal USA Products Inc
Category: otc | Type: HUMAN OTC DRUG LABEL
Date: 20260107

ACTIVE INGREDIENTS: DROMETRIZOLE TRISILOXANE 70 mg/1 mL; BEMOTRIZINOL 50 mg/1 mL; OCTISALATE 50 mg/1 mL; OCTOCRYLENE 50 mg/1 mL; AVOBENZONE 30 mg/1 mL; HOMOSALATE 20 mg/1 mL; ENSULIZOLE 5 mg/1 mL
INACTIVE INGREDIENTS: WATER; ALCOHOL; SILICON DIOXIDE; ISOPROPYL MYRISTATE; GLYCERIN; DIISOPROPYL SEBACATE; PROPANEDIOL; PERLITE; .ALPHA.-TOCOPHEROL, DL-; TROLAMINE; CAPRYLYL GLYCOL; TRISODIUM ETHYLENEDIAMINE DISUCCINATE; HYDROXYETHYL CELLULOSE, UNSPECIFIED; ACRYLATES/C10-30 ALKYL ACRYLATE CROSSPOLYMER (60000 MPA.S); PENTYLENE GLYCOL; BUTYLENE GLYCOL; CITRIC ACID MONOHYDRATE

Drug Facts

Active ingredient

Drometrizole trisiloxane 7%

Bemotrizinol 5%

Octisalate 5%

Octocrylene 5%

Avobenzone 3%

Homosalate 2%

Ensulizole 0.5%

Purpose

Sunscreen

Warnings

For external use only

Do not use

on broken skin.

When using this product

avoid contact with eyes. If contact occurs, rinse thoroughly with water.

Stop use and ask a doctor

if rash occurs.

Keep out of reach of children.

If swallowed, call a poison control centre or get medical help right away.

Directions

Adults and adolescents 12 to 17 years.

- Apply generously and evenly 15 minutes before sun exposure
- Reapply at least every 2 hours
- Reapply after 80 minutes of siwmming or sweating
- Reapply immediately after towel drying
- Sun Protection Measures:

Spending time in the sun increases your risk of skin cancer and early skin aging. To decrease this risk:

- regularly use a Broad Spectrum SPF 15 or higher sunscreen
- limit time in the sun, especially from 10 a.m. - 2 p.m.
- wear long-sleeved shirts, pants, hats, and sunglasses.

Inactive ingredients

water, alcohol denat., silica, , isopropyl myristate, glycerin, diisopropyl sebacate, propanediol, c12-22 alkyl acrylate/hydroxyethylacrylate copolymer, perlite, dl-alpha tocopherol, triethanolamine, caprylyl glycol, trisodium ethylenediamine disuccinate, hydroxyethylcellulose, acrylate/c10-30 alkyl acrylate crosspolymer, pentylene glycol, butylene glycol, citric acid

Questions?

1 888-966-2735

(9-Ombrel)